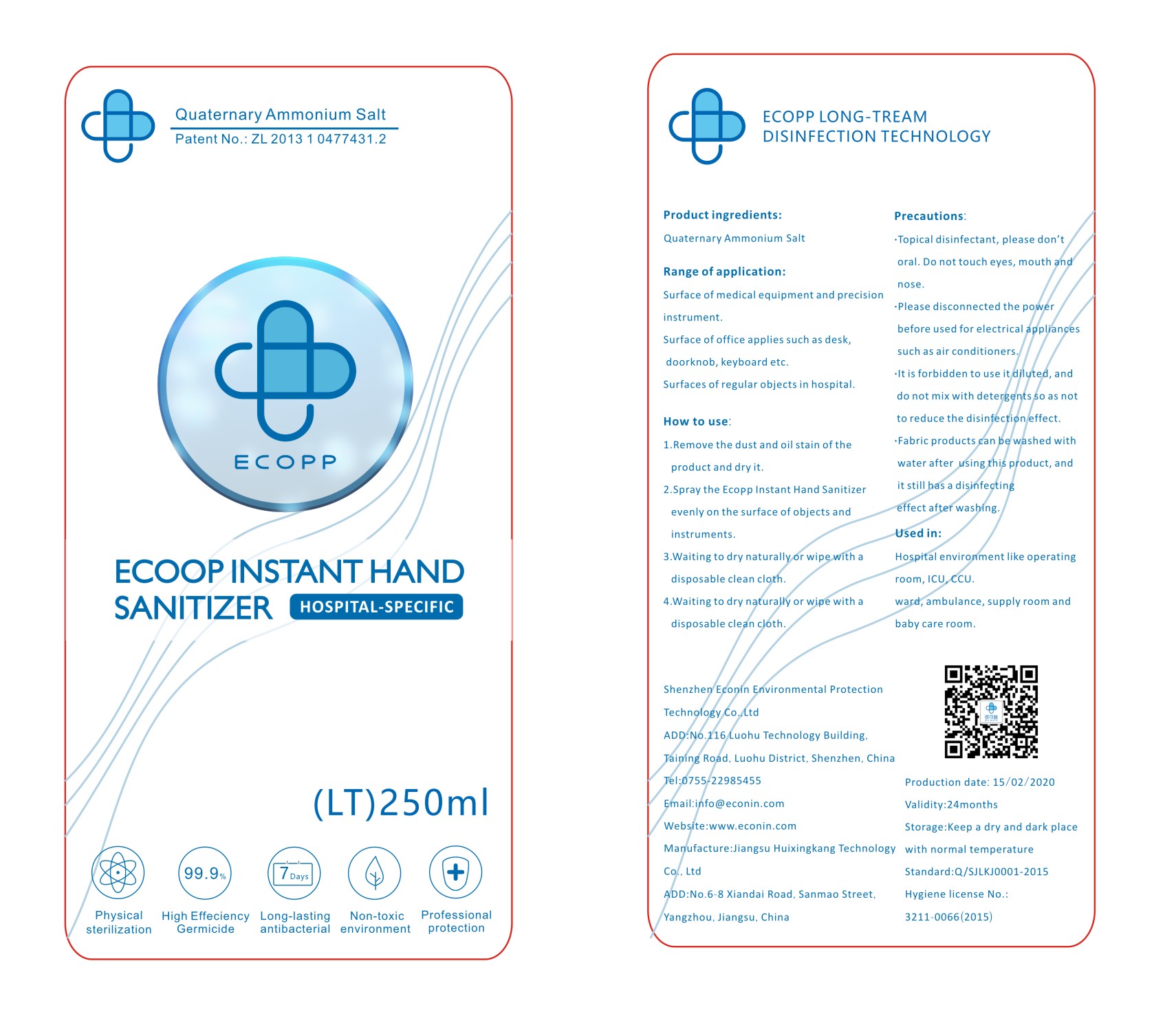 DRUG LABEL: ecopp long acting antibacterial disinfectant
NDC: 42134-005 | Form: LIQUID
Manufacturer: Shenzhen Econin Environmental Protection Technology Co., Ltd.
Category: otc | Type: HUMAN OTC DRUG LABEL
Date: 20200428

ACTIVE INGREDIENTS: BENZALKONIUM CHLORIDE 0.01 mg/250 mL
INACTIVE INGREDIENTS: AMMONIUM CHLORIDE 0.05 mg/250 mL; WATER

WARNINGS

Topical disinfectant, please don't oral. Do not touch eyes, mouth and nose.

Please disconnected the power before used for electrical appliances such as air conditioners .
It is forbidden to use itdiluted, and do not mix with detergents so as not to reduce the disinfection effect.
Fabric products can be washed with water after using this product, and it still has a disinfecting effect after washing.

PURPOSE

Disinfection
Sterilization
No Rinseing

keep out of reach of children

INDICATIONS AND USAGE

Remove the dust and oil stain of the product and dry it.
Spray the Ecoop Instant Hand Sanitizer evenly on the surface of objects and instruments.
Waiting to dry naturallyor wipe with a disposable clean cloth.

INACTIVE INGREDIENT

benzalkonium chloride, water

ACTIVE INGREDIENT

0.18% - 0.22% Behenyl Trimethyl Ammonium Chloride

DOSAGE AND ADMINISTRATION

Surface of medical equipment and precisic instrument.
Surface of office applies such as desk,doorknob, keyboard etc.
Surfaces of regular objects in hospital.